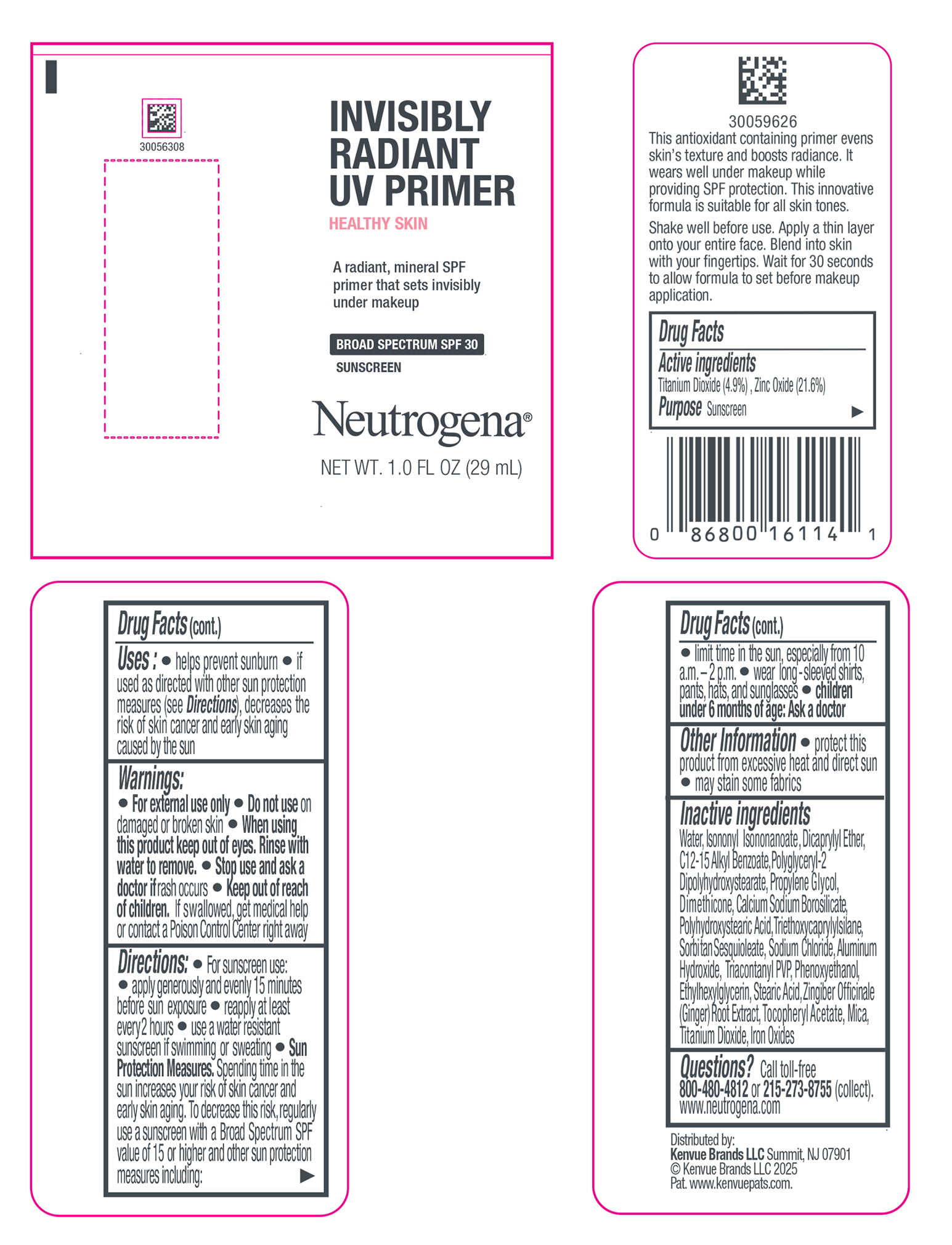 DRUG LABEL: Neutrogena Healthy Skin Invisibly Radiant UV Primer SPF 30
NDC: 69968-0900 | Form: LOTION
Manufacturer: Kenvue Brands LLC
Category: otc | Type: HUMAN OTC DRUG LABEL
Date: 20250218

ACTIVE INGREDIENTS: ZINC OXIDE 216 mg/1 mL; TITANIUM DIOXIDE 49 mg/1 mL
INACTIVE INGREDIENTS: DICAPRYLYL ETHER; FERROUS OXIDE; PROPYLENE GLYCOL; SODIUM CHLORIDE; ALUMINUM HYDROXIDE; STEARIC ACID; POLYHYDROXYSTEARIC ACID (2300 MW); ALPHA-TOCOPHEROL ACETATE; WATER; ISONONYL ISONONANOATE; ALKYL (C12-15) BENZOATE; DIMETHICONE; SORBITAN SESQUIOLEATE; PHENOXYETHANOL; GINGER; ETHYLHEXYLGLYCERIN; TRICONTANYL POVIDONE; MICA; TRIETHOXYCAPRYLYLSILANE; POLYGLYCERYL-2 DIPOLYHYDROXYSTEARATE; CALCIUM SODIUM BOROSILICATE

Neutrogena Healthy Skin Invisibly Radiant UV Primer SPF 30

Drug Facts

Active ingredient

Titanium Dioxide (4.9%), Zinc Oxide (21.6%)

Purpose

Sunscreen

Uses

- helps prevent sunburn
- if used as directed with other sun protection measures (see Directions), decreases the risk of skin cancer and early skin aging caused by the sun

Warnings

- For external use only

- Do not use on damaged or broken skin

- When using this product keep out of eyes. Rinse with water to remove.

- Stop use and ask a doctor if rash occurs

- Keep out of reach of children. If swallowed get medical help or contact a Poison Control Center right away

Directions

For sunscreen use:

- apply generously and evenly 15 minutes before sun exposure
- reapply at least every 2 hours
- use a water resistant sunscreen if swimming or sweating
- Sun protection Measures. Spending time in the sun increases your risk of skin cancer and early skin aging. To decrease this risk, regularly use a sunscreen with a Broad Spectrum SPF value of 15 or higher and other sun protection measures including:
  - limit time in the sun, especially from 10 a.m. – 2 p.m.
  - wear long-sleeved shirts, pants, hats, and sunglasses
- children under 6 months of age: Ask a doctor

Other Information

- protect this product from excessive heat and direct sun
- may stain some fabrics

Inactive ingredients

Water, Isononyl Isononanoate,Dicaprylyl Ether, C12-15 Alkyl Benzoate, Polyglyceryl-2 Dipolyhydroxystearate, Propylene Glycol, Dimethicone, Calcium Sodium Borosilicate, Polyhydroxystearic Acid,Triethoxycaprylylsilane, Sorbitan Sesquioleate, Sodium Chloride, Aluminum Hydroxide, Triacontanyl PVP, Phenoxyethanol, Ethylhexylglycerin, Stearic Acid, Zingiber Officinale (Ginger) Root Extract, Tocopheryl Acetate, Mica, Titanium Dioxide, Iron Oxides

Questions?

Call toll-free 800-480-4812 or 215-273-8755 (collect).

www.neutrogena.com

Distributed by:
Kenvue Brands LLC
Summit, NJ 07901

PRINCIPAL DISPLAY PANEL - 29 mL Tube Label

INVISIBLY

RADIANT

UV PRIMER

HEALTHY SKIN

A radiant, mineral SPF

primer that sets invisibly

under makeup

BROAD SPECTRUM SPF 30

SUNSCREEN

Neutrogena®

NET WT. 1.0 FL OZ (29 mL)